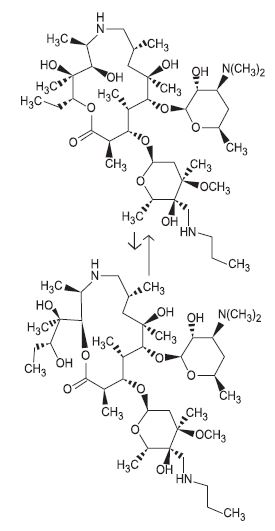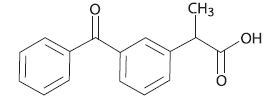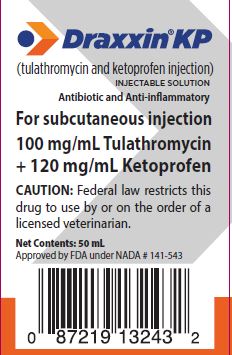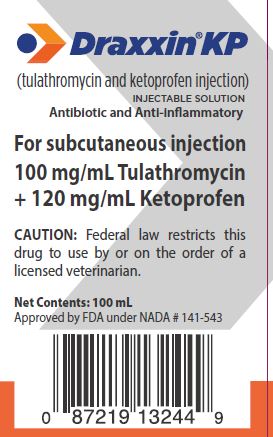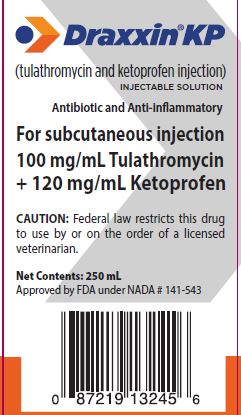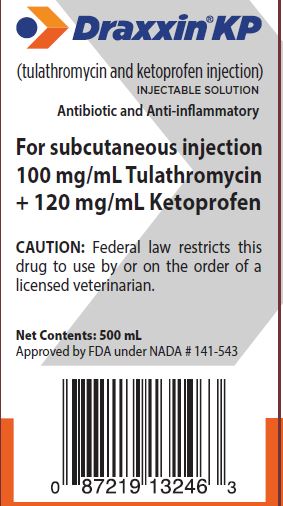 DRUG LABEL: Draxxin KP
NDC: 54771-2155 | Form: INJECTION, SOLUTION
Manufacturer: Zoetis Inc.
Category: animal | Type: PRESCRIPTION ANIMAL DRUG LABEL
Date: 20260127

ACTIVE INGREDIENTS: TULATHROMYCIN 100 mg/1 mL; KETOPROFEN 120 mg/1 mL

Draxxin® KP

Draxxin® KP
(tulathromycin and ketoprofen injection)
INJECTABLE SOLUTION
Antibiotic and Anti-inflammatory

For subcutaneous injection
100 mg/mL Tulathromycin + 120 mg/mL Ketoprofen

For subcutaneous injection
Antibiotic:
100 mg of Tulathromycin/mL
Non-Steroidal Anti-inflammatory Drug:
120 mg Ketoprofen/mL

CAUTION

Federal law restricts this drug to use by or on the order of a licensed veterinarian.

DESCRIPTION

DRAXXIN KP (tulathromycin and ketoprofen injection) Injectable Solution is a ready to use sterile parenteral preparation containing tulathromycin, a semi- synthetic macrolide antibiotic of the subclass triamilide and ketoprofen a non-steroidal anti-inflammatory drug. ACTIVE INGREDIENTS: Each mL of DRAXXIN KP contains 100 mg of tulathromycin as a free base and 120 mg ketoprofen as a free acid in a 50% propylene glycol vehicle.
INACTIVE INGREDIENTS:
monothioglycerol (5 mg/mL), 2-pyrrolidone (70 mg/mL), citric acid (20 mg/mL) and sodium hydroxide/hydrochloric acid added to adjust pH.
DRAXXIN KP contains an equilibrated mixture of two isomeric forms of tulathromycin in a 9:1 ratio and a racemic mixture of ketoprofen.
The structures of the tulathromycin isomers and ketoprofen are shown below:

Figure 1. Tulathromycin structures
The chemical names of the tulathromycin isomers are (2R,3S, 4R,5R,8R,10R,11R,12S, 13S,14R)-13-[[2,6-dideoxy-3-C-methyl-3-Ο-methyl-4-C-[(propylamino) methyl]-α-L-ribo-hexopyranosyl]oxy]-2-ethyl-3,4,10-trihydroxy-3,5,8,10,12, 14-hexamethyl-11-[[3,4,6-trideoxy-3-(dimethylamino)-β-D-xylohexopyranosyl]-oxy]-1-oxa-6-azacyclopentadecan-15-one and (2R, 3R,6R,8R,9R,10S,11S,12R)- 11-[[2,6-dideoxy-3-C-methyl-3-Ο-methyl-4-C-[(propylamino)methyl]-α-L-ribohexopyranosyl]oxy]-2-[(1S,2R)-1,2-dihydroxy-1-methylbutyl]-8-hydroxy-3,6,8,10,12-pentamethyl-9-[[3,4,6-trideoxy -3-(dimethylamino)-β-D-xylo-hexopyranosyl]oxy]-1-oxa-4-azacyclotridecan-13-one, respectively.
Figure 2. Ketoprofen Structure
The chemical name of ketoprofen is 2-(3-Benzoylphenyl) propanoic acid.

INDICATIONS

Draxxin® KP is indicated for the treatment of bovine respiratory disease (BRD) associated with Mannheimia haemolytica, Pasteurella multocida, Histophilus somni, and Mycoplasma bovis, and control of pyrexia associated with BRD in beef steers, beef heifers, beef calves 2 months of age and older, beef bulls, dairy bulls, and replacement dairy heifers. Not for use in reproducing animals over one year of age, dairy calves, or veal calves.

DOSAGE AND ADMINISTRATION

Inject subcutaneously as a single dose in the neck at a dosage of 2.5 mg tulathromycin and 3 mg ketoprofen/kg (1.1 mL/100 lb) bodyweight (BW). Do not inject more than 10 mL per injection site. Use this product within 56 days of the first puncture and puncture a maximum of 20 times. If more than 20 punctures are anticipated, the use of automatic injection equipment or a repeater syringe is recommended. When using a draw-off spike or needle with bore diameter larger than 16 gauge, discard any product remaining in the vial immediately after use.

Table 1. DRAXXIN KP Cattle Dosing Guide

Animal Weight (lb) | Dose Volume (mL)
150 | 1.7
200 | 2.3
250 | 2.8
300 | 3.4
350 | 4.0
400 | 4.5
500 | 5.7
600 | 6.8
700 | 8.0
800 | 9.1
900 | 10.2
1000 | 11.4

CONTRAINDICATIONS

The use of DRAXXIN KP Injection is contraindicated in animals previously found to be hypersensitive to tulathromycin and ketoprofen.

WITHDRAWAL PERIODS AND RESIDUE WARNINGS

Cattle must not be slaughtered for human consumption within 18 days following last treatment with this drug product. Not for use in female dairy cattle 1 year of age or older, including dry dairy cows; use in these cattle may cause drug residues in milk and/or in calves born to these cows or heifers. Not for use in beef calves less than 2 months of age, dairy calves, and veal calves. A withdrawal period has not been established for this product in pre-ruminating calves.

USER SAFETY WARNINGS

NOT FOR HUMAN USE. KEEP OUT OF REACH OF CHILDREN.
The Safety Data Sheet (SDS) provides more detailed occupational safety information. To obtain a Safety Data Sheet contact Zoetis Inc. at 1-888-963-8471.

ANIMAL SAFETY WARNINGS and PRECAUTIONS

The effects of DRAXXIN KP on bovine reproductive performance, pregnancy, and lactation have not been determined. Not for use in reproducing animals over one year of age because reproductive safety testing has not been conducted. Administration of tulathromycin and ketoprofen injection may result in injection site swelling that appears the day after treatment and may persist for at least 32 days post-injection. This may result in trim loss of edible tissue at slaughter.
As a class, cyclo-oxygenase inhibitory NSAIDs (Ketoprofen) may be associated with gastrointestinal, hepatic and renal toxicity. Sensitivity to drug-associated adverse effects varies with the individual patient. Patients at greatest risk for renal toxicity are those that are dehydrated, on concomitant diuretic therapy, or those with renal, cardiovascular, and/or hepatic dysfunction. Use judiciously when renal impairment or gastric ulceration is suspected.
Since many NSAIDs possess the potential to induce gastrointestinal ulceration, concomitant use of DRAXXIN KP with other anti-inflammatory drugs, such as other NSAIDs and corticosteroids, should be avoided or closely monitored. Discontinue use if fecal blood is observed.

ADVERSE REACTIONS

Repeated administration of NSAIDs can result in gastric or renal toxicity. Sensitivity to drug-associated adverse effects varies with the individual patient. Patients at greatest risk for toxicity are those that are dehydrated, on concomitant diuretic therapy, or those with pre-existing gastric ulcers, renal, cardiovascular, and/or hepatic dysfunction.

CONTACT INFORMATION

To report suspected adverse drug experiences, to obtain a Safety Data Sheet (SDS) or for technical assistance, contact Zoetis at (888) 963-8471. For additional information about adverse drug experience reporting for animal drugs, contact the FDA at 1-888-FDA-VETS or http://www.fda.gov/reportanimalae.

CLINICAL PHARMACOLOGY

Mechanism of Action
Ketoprofen is a propionic acid derivate and nonsteroidal anti-inflammatory drug (NSAID) with anti-inflammatory, analgesic and antipyretic effects. Ketoprofen inhibits the activity of the enzymes cyclo-oxygenase I and II, resulting in a decreased formation of precursors of prostaglandins and thromboxanes. Ketoprofen also causes a decrease in the formation of thromboxane A2 synthesis, by thromboxane synthase, thereby inhibiting platelet aggregation. The principal mechanism of action of tulathromycin against bacteria involves direct inhibition of essential protein biosynthesis by selective binding to bacterial 50S ribosomal subunits. Tulathromycin acts by stimulating the dissociation of peptidyl- tRNA from the ribosome during the translocation process.
Clinical Pharmacology
In a GLP pharmacokinetic study, 60 cattle received one of 3 treatments: 2.5 mg tulathromycin/kg BW, 3 mg ketoprofen/kg BW or a combination of the two active ingredients (2.5 mg tulathromycin and 3 mg of ketoprofen/kg BW) via subcutaneous injection. Blood samples were obtained pre-dose and at 20 min, 40 min, 1, 1.5, 2, 3, 4, 6, 10, 24, 28, 32, 48, 52, 56, 72, 120, 168, 216, 264, 336, and 360 hours after dosing. The samples were analyzed using validated highperformance liquid chromatography-mass spectrometry (LC-MS/MS) methods for tulathromycin and ketoprofen concentrations. The rate of drug exposure was greater for the ketoprofen alone product.

The mean [±standard deviation (SD)] maximum plasma concentration (Cmax) and time to Cmax (tmax) was 6451 (±1342) ng/mL and 0.83 (±0.53) hr, respectively for ketoprofen alone compared to a mean (±SD) Cmax and tmax of 2322 (±1505) ng/mL and 4.0 (±2.93) hr, respectively, for ketoprofen in the combination product. However, the extent of drug exposure was slightly greater and terminal half life (t1/2) was longer for ketoprofen in the combination product. The mean (±SD) area under the drug concentration- time curve between times 0 and the last quantifiable concentration (AUC0-t(last)) was 26458 (±3605) ng*hr/mL for ketoprofen in the combination product and 23106 (±3500) for ng*hr/mL for ketoprofen alone. Similarly, the mean t 1/2 was 6.84 (±2.09) hr for ketoprofen in the combination product and 2.86 (±1.09) hr for ketoprofen alone. Although the mean (±SD) Cmax of tulathromycin in the combination group (373 (±105) ng/mL) was less than tulathromycin alone (653 (±261) ng/mL), based on mean (±SD) AUC0-t(last), the combination (13647 (±2577) ng*hr/mL) and tulathromycin alone (14088 (±4408) ng*hr/mL) groups had similar tulathromycin bioavailability.

Tulathromycin half life was also similar between the combination (93.3 (±27.9) hr) and tulathromycin alone (98.7 (±23.1) hr) groups.

MICROBIOLOGY

Based on data provided for the approval of Draxxin® (tulathromycin injection, NADA 141-244), tulathromycin has demonstrated in vitro activity against Mannheimia haemolytica, Pasteurella multocida, Histophilus somni, and Mycoplasma bovis, four pathogens associated with BRD.

TARGET ANIMAL SAFETY

Thirty-two (16 male and 16 female) growing cattle were enrolled in a margin of safety study. Calves were injected subcutaneously with either saline, DRAXXIN KP at the label dose 2.5 mg tulathromycin/3 mg ketoprofen/kg BW, DRAXXIN KP at 3 times the label dose, or DRAXXIN KP at 5 times the label dose. Calves received three doses at a 14-day interval between doses. Daily clinical observations were conducted by a veterinarian as well as daily general health observations and injection site evaluations. Samples were collected for urinalysis, fecal occult blood, hematology, serum chemistry and coagulation and for pharmacokinetics. At the conclusion of the study, all animals were euthanized and necropsied for gross pathology and histopathology evaluation. Injection site lesion volumes for the first injection site was calculated. Injection site reactions were noted in all DRAXXIN KP-treated animals and the size and incidence of injection site lesions were greater in the 3X and 5X treatment groups. Test article-related differences in serum chemistry parameters were lower alkaline phosphatase in the 5X group; lower albumin in the 3X and 5X groups; lower total protein (TP) and serum calcium in the 1X, 3X and 5X groups; and higher creatine kinase (CK) in the 1X, 3X, and 5X groups. The changes for serum calcium and albumin were considered clinically insignificant because all values were within the normal reference range on the days with statistical differences. The changes for TP were considered secondary to the differences in albumin and clinically insignificant because the albumin changes were considered clinically insignificant. In addition, the only TP values that were outside of the normal reference range were only 0.1 g/dL below the normal reference range. The differences in neutrophil values might be secondary to test article-associated injection site inflammation and the differences in CK values are directly associated with injection site reactions. There were non-quantifiable ketoprofen plasma concentrations prior to the second and third doses, while there was a modest accumulation for tulathromycin (mean ≤16.5%) with the 14-day dosing interval. There was dose proportional increase in tulathromycin AUC0-t(last) with an increase in dose, while there was slightly greater than dose proportional increase in ketoprofen AUC0- t(last). A single calf in Group T04 had test article-associated positive fecal occult blood samples on Days 15 and 29. Microscopic mucosal erosions of the pylorus of the abomasum were present in the 3X (2/8) and 5X (1/8) groups and was considered test article-related. Renal interstitial inflammation and minimal multifocal degeneration and regeneration occurred at similar incidence and severity in treated and control calves.

Subcutaneous injection of cattle with tulathromycin- ketoprofen at the label dose was well tolerated.

EFFECTIVENESS

A multi-location field study was conducted to evaluate the effectiveness of Draxxin® KP for the treatment of bovine respiratory disease (BRD) associated with Mannheimia haemolytica, Pasteurella multocida, Histophilus somni, and Mycoplasma bovis, and control of pyrexia associated with BRD. A total of 819 cattle with clinical signs of BRD (moderate depression and respiratory distress, and a rectal temperature ≥104.5 °F) were enrolled and treated with either saline (0.025 mL/kg BW), tulathromycin (2.5 mg/kg BW) or Draxxin® KP (2.5 mg tulathromycin/kg BW and 3 mg ketoprofen/kg BW) administered by subcutaneous injection. Rectal temperatures were measured six hours later and animals were observed for clinical signs of BRD through 14 days post-treatment. An animal was classified as a treatment success for treatment of BRD if it was not classified as a failure prior to Day 14, and had normal or mild depression and respiratory distress scores and a rectal temperature <104.5 °F on Day 14. An animal was classified as a treatment success for control of pyrexia associated with BRD if it displayed a ≥2 °F reduction in rectal temperature at 6- hours post-treatment compared to pre-treatment. The Draxxin® KP-treated group had a significantly different (P=0.0020) and numerically higher success rate (76.2%) for the treatment of BRD compared to the saline-treated group (31.6%), and the success rate in the Draxxin® KP-treated group was statistically non-inferior to that in the group receiving tulathromycin alone. The success rate (back-transformed estimate) for pyrexia associated with BRD in the Draxxin® KP-treated group was significantly different (P=0.0010) and numerically higher (83.8%) at 6 hours post-treatment than the success rate in the saline-treated group (2.4%). The success rate (back-transformed estimate) for pyrexia associated with BRD in the Draxxin® KP-treated group was significantly different (P=0.0032) and numerically higher (83.9%) at 6 hours post-treatment than the success rate in the tulathromycin-treated group (5.4%). A sufficient number of Mannheimia haemolytica, Pasteurella multocida, Histophilus somni, and Mycoplasma bovis were isolated from cattle in the study to demonstrate that these BRD pathogens were contributing to the observed disease.

HOW SUPPLIED

DRAXXIN KP Injection is available in the following package sizes:
50 mL vial
100 mL vial
250 mL vial
500 mL vial

STORAGE CONDITIONS

Store at or below 25°C (77°F), with excursions up to 40°C (104°F). Protect from freezing.

APPROVED BY FDA under NADA # 141-543
zoetis
Distributed by:
Zoetis Inc.
Kalamazoo, MI 49007
Product of Spain
October 2024
40035963

PRINCIPAL DISPLAY PANEL - 50 mL Carton

40028877

PRINCIPAL DISPLAY PANEL - 100 mL Carton

40035967

PRINCIPAL DISPLAY PANEL - 250 mL Carton

40028874

PRINCIPAL DISPLAY PANEL - 500 mL Carton

40028869